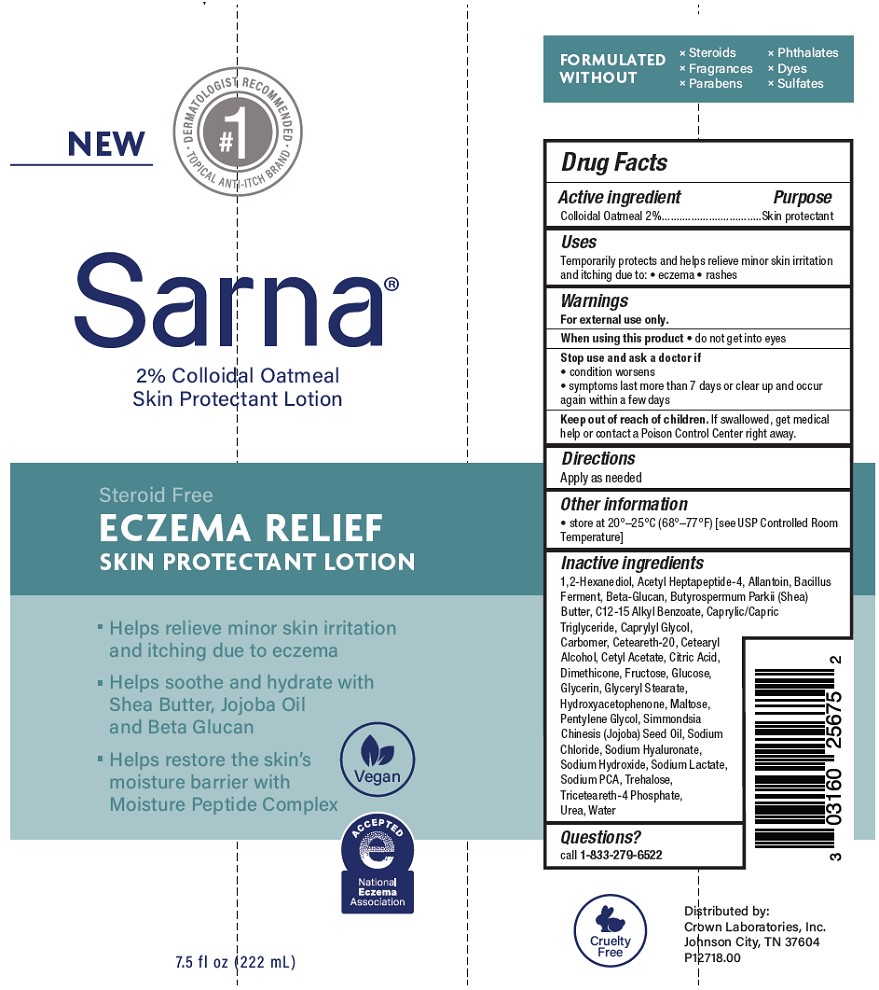 DRUG LABEL: Sarna
NDC: 0316-0256 | Form: LOTION
Manufacturer: Crown Laboratories, Inc.
Category: otc | Type: HUMAN OTC DRUG LABEL
Date: 20260112

ACTIVE INGREDIENTS: OATMEAL 20 mg/1 mL
INACTIVE INGREDIENTS: ACETYL HEPTAPEPTIDE-4; YEAST .BETA.-D-GLUCAN; C12-15 ALKYL BENZOATE; SODIUM PCA; FRUCTOSE; GLYCERYL STEARATE; CETYL ACETATE; CAPRYLYL GLYCOL; CAPRYLIC/CAPRIC TRIGLYCERIDE; CETEARYL ALCOHOL; DIMETHICONE; SIMMONDSIA CHINENSIS (JOJOBA) SEED OIL; SODIUM CHLORIDE; SODIUM HYALURONATE; TRICETEARETH-4 PHOSPHATE; CITRIC ACID; GLUCOSE; HYDROXYACETOPHENONE; CETEARETH-20; SODIUM HYDROXIDE; CARBOMER INTERPOLYMER TYPE A (55000 CPS); ALLANTOIN; 1,2-HEXANEDIOL; BUTYROSPERMUM PARKII (SHEA) BUTTER; SODIUM LACTATE; TREHALOSE; UREA; WATER; PENTYLENE GLYCOL; GLYCERIN; MALTOSE

Sarna Eczema Relief Skin Protectant Lotion

Active ingredient

Colloidal Oatmeal 2%

Purpose

Skin protectant

Uses

Temporarily protects and helps relieve minor skin irritation and itching due to: • eczema • rashes

Warnings

For external use only.

When using this product

- do not get into eyes

Stop use and ask a doctor if

- condition worsens
- symptoms last more than 7 days or clear up and occur again within a few days

Keep out of reach of children.

If swallowed, get medical help or contact a Poison Control Center right away.

Directions

Apply as needed

Other information

- store at 20°–25°C (68°–77°F) [see USP Controlled Room Temperature]

Inactive ingredients

1,2-Hexanediol, Acetyl Heptapeptide-4, Allantoin, Bacillus Ferment, Beta-Glucan, Butyrospermum Parkii (Shea) Butter, C12-15 Alkyl Benzoate, Caprylic/Capric Triglyceride, Caprylyl Glycol, Carbomer, Ceteareth-20, Cetearyl Alcohol, Cetyl Acetate, Citric Acid, Dimethicone, Fructose, Glucose, Glycerin, Glyceryl Stearate, Hydroxyacetophenone, Maltose, Pentylene Glycol, Simmondsia Chinesis (Jojoba) Seed Oil, Sodium Chloride, Sodium Hyaluronate, Sodium Hydroxide, Sodium Lactate, Sodium PCA, Trehalose, Triceteareth-4 Phosphate, Urea, Water

Questions?

call 1-833-279-6522

PACKAGE LABEL

#1 DERMATOLOGIST RECOMMENDED TOPICAL ANTI-ITCH BRAND

Sarna

2% Colloidal Oatmeal

Skin Protectant Lotion

Stroid Free

ECZEMA RELIEF

SKIN PROTECTANT LOTION

- Helps relieve minor skin irritation and ithcing due to eczema
- Helps soothe and hydrate with Shea Butter, Jojoba Oil and Beta Glucan
- Helps restore the skin's moisture barrier with Moisture Peptide Complex

Vegan

Accepted National Eczema Association

7.5 fl oz (222 ml)

Cruelty Free

Distributed by: Crown Laboratories, Inc.

Johnson City, TN 37604

P12718.00